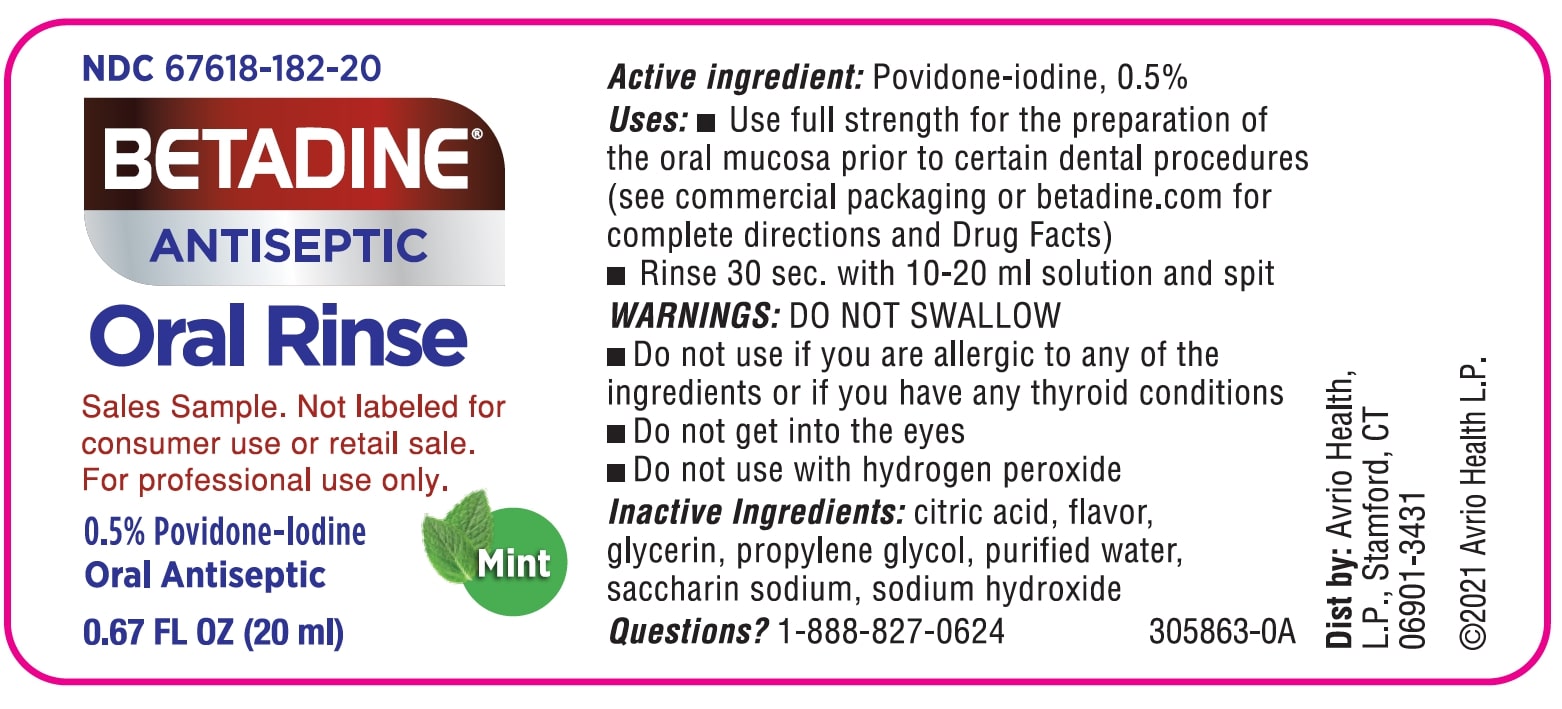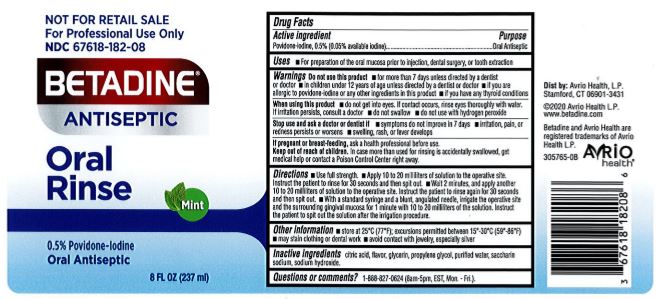 DRUG LABEL: Povidone Iodine
NDC: 0395-9136 | Form: LIQUID
Manufacturer: Humco Holding Group, Inc.
Category: otc | Type: HUMAN OTC DRUG LABEL
Date: 20231215

ACTIVE INGREDIENTS: POVIDONE-IODINE 5 mg/1 mL
INACTIVE INGREDIENTS: MENTHOL; SACCHARIN SODIUM; ANHYDROUS CITRIC ACID; GLYCERIN; SODIUM HYDROXIDE; WATER; PROPYLENE GLYCOL; PEPPERMINT

Private Label Povidone Iodine Oral Rinse 0.5%

Drug Facts

Active Ingredient

Povidone-Iodine 0.5%

(0.05% available iodine)

Purpose

Oral Antiseptic

Use

For preparation of the oral mucosa prior to injection, dental surgery or tooth extraction.

Warnings

Do not use this product

- for more than 7 days unless directed by a dentist of doctor
- in children under 12 years of age unless directed by a dentist or doctor
- if you are allergic to povidone-iodine or any other ingredients in this product
- if you have any thyroid conditions

Stop use and consult a doctor if

Symptoms do not improve in 7 days.

Irritation, pain or redness persists or worsens.

Swelling, rash or fever develops.

When using this product do not

Get into eyes. If contact occurs, rinse eyes thoroughly with water. If iritation persists, consult a doctor.

Swallow.

Use with hydrogen peroxide.

Keep out of reach of children.

In case more than used for rinsing is accidentally swallowed, get medical help or contact a Poison Control Center right away.

Directions

- Use full strength.
- Apply 10 to 20 milliliters of solution to the operative site. Instruct the patient to rinse for 30 seconds and then spit out.
- Wait 2 minutes, and apply another 10 to 20 milliliters of solution to the operative site. Instruct the patient to rinse again for 30 seconds and then spit out.
- With a standard syringe and a blunt, angulated needle, irrigate the operative site and the surrounding gingival mucosa for 1 minute with 10 to 20 milliliters of the solution. Instruct the patient to spit out the solution after the irrigation procedure.

Other information

- Store at 25°C (77°F); Excursions permitted between 15°C and 30°C (59°F-86°F).
- May stain clothing or dental work.
- Avoid contact with jewelry, especially silver.

Inactive Ingredients

Citric acid, flavor, glycerin, propylene glycol, purified water, saccarin sodium, sodium hydroxide.

Do not use this product

- For more than 7 days unless directed by a dentist or doctor.
- If you are allergic to povidone-iodine or any other ingredients in this product.
- If you have any thyroid conditions.

If pregnant or breast-feeding

Ask a health professional before use.